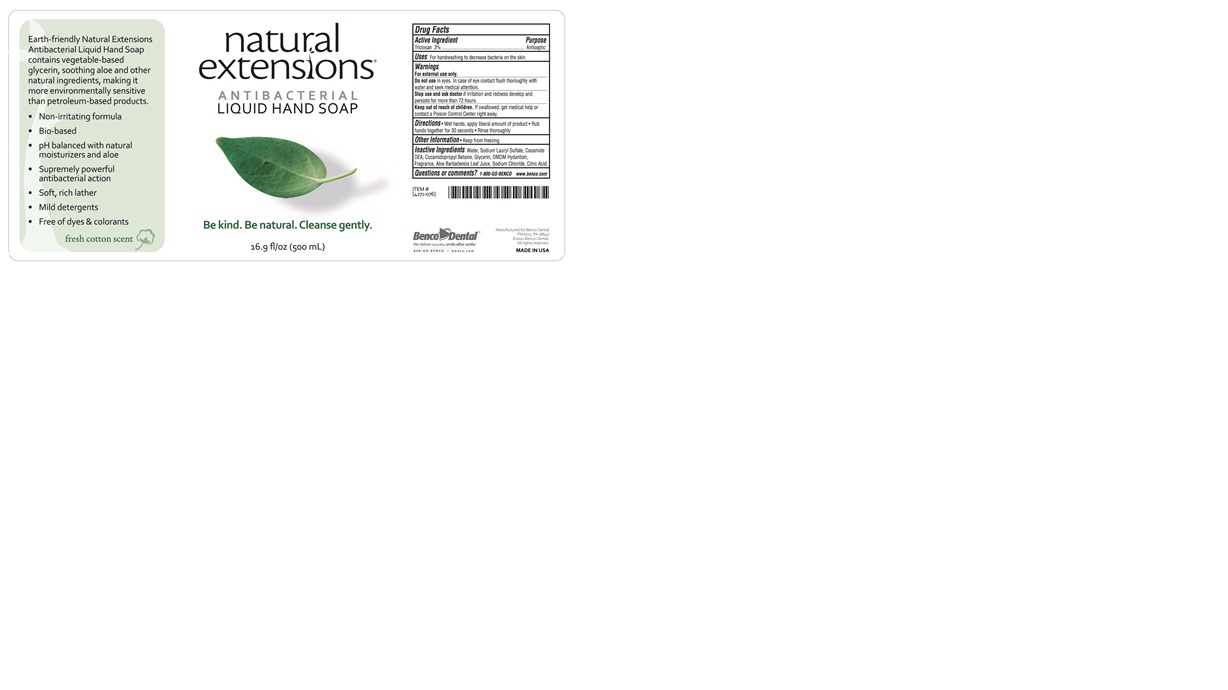 DRUG LABEL: natural extensions Antibacterial Liquid Hand Wash
NDC: 66975-102 | Form: SOAP
Manufacturer: Benco Dental Company
Category: otc | Type: HUMAN OTC DRUG LABEL
Date: 20120321

ACTIVE INGREDIENTS: TRICLOSAN 3 mL/1000 mL
INACTIVE INGREDIENTS: WATER; SODIUM LAURYL SULFATE; COCO DIETHANOLAMIDE; COCAMIDOPROPYL BETAINE; GLYCERIN; DMDM HYDANTOIN; ALOE VERA LEAF; SODIUM CHLORIDE; CITRIC ACID MONOHYDRATE

natural extensions Antibacterial Liquid Hand Soap

Earth-friendly Natural Extensions Antibacterial Liquid Hand Soap contains vegetable-based glycerin, soothing aloe and other natural ingredients, making it more environmentally sensitive than petroleum-based products.

- Non-irritating formula
- Bio-based
- pH balanced with natural moisturizers and aloe
- Supremely powerful antibacterial action
- Soft, rich lather
- Mild detergents

Active Ingredient

Triclosan.3%

Purpose

Antiseptic

WARNINGS

For external use only.

Do not use in eyes. In case of eye contact flush thoroughly with water and seek medical attention.

Stop use and ask doctor if irritation and redness develop and persists for more than 72 hours.

KEEP OUT OF REACH OF CHILDREN

Keep out of the reach of children. If swallowed, get medical help or contact a Poison Control Center right away.

Other Information

- Keep from freezing

Inactive Ingredients

Water, Sodium Lauryl Sulfate, Cocamide DEA, Cocamidopropyl Betaine, Glycerin, DMDM Hydantoin, Fragrance, Aloe Barbadensis Leaf Juice, Sodium Chloride, Citric Acid.

Questions or comments? 1-800-GO-BENCO www.benco.com

PACKAGE LABEL

500 ml Pump Bottle

Directions

Wet hands. Apply liberal amount of product. Rub hands together for 30 seconds. Rinse thoroughly.

Uses

For handwashing to decrease bacteria on the skin.